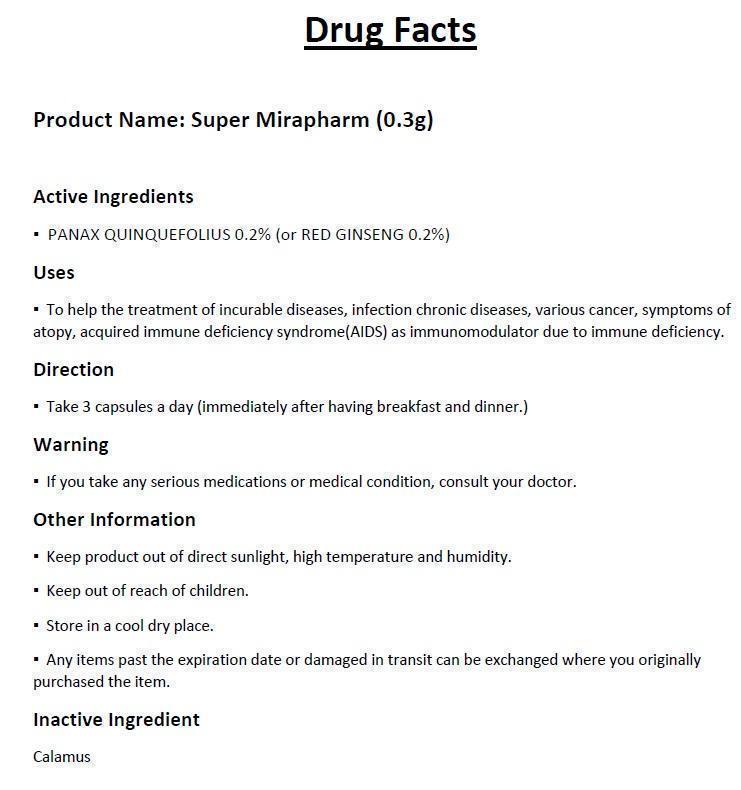 DRUG LABEL: SUPER MIRAPHARM (0.3g)
NDC: 61065-1002 | Form: CAPSULE
Manufacturer: MIRAPHARM., Inc.
Category: otc | Type: HUMAN OTC DRUG LABEL
Date: 20150414

ACTIVE INGREDIENTS: PANAX QUINQUEFOLIUS WHOLE 0.0006 g/1 1
INACTIVE INGREDIENTS: ACORUS CALAMUS ROOT

SUPER MIRAPHARM (0.3g)

Active ingredients

- PANAX QUINQUEFOLIUS 0.2% (or RED GINSENG 0.2%)

Purpose:

Stimulant

Keep out of reach of children.

Uses

- To help the treatment of incurable diseases, infection chronic diseases, various cancer, symptoms of atopy, acquired immune deficiency syndrome (AIDS) as immunomodulator due to immune deficiency.

Warning

- If you take any serious medications or medical condition, consult your doctor.

Direction

- Take 3 capsules a day (immediately after having breakfast and dinner.)

Other Information

- Keep product out of direct sunlight, high temperature and humidity.
- Store in a cool dry place.
- Any items past the expiration date or damaged in transit can be exchanged where you originally purchased the item.

Inactive Ingredient

Calamus